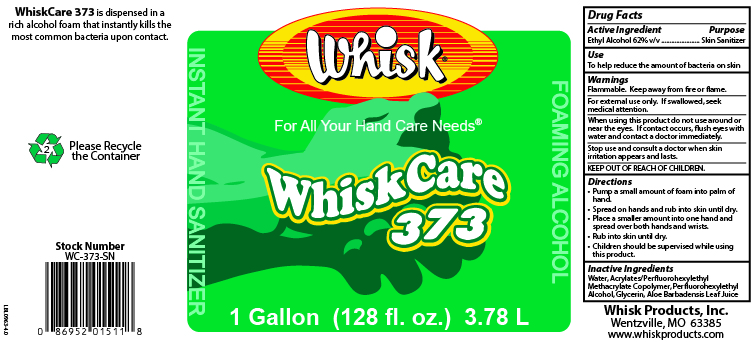 DRUG LABEL: WhiskCare 373
NDC: 65585-374 | Form: SOAP
Manufacturer: Whisk Products, Inc.
Category: otc | Type: HUMAN OTC DRUG LABEL
Date: 20240708

ACTIVE INGREDIENTS: ALCOHOL 620 mL/1 L
INACTIVE INGREDIENTS: BUTYL ACRYLATE/METHYL METHACRYLATE/PERFLUOROHEXYLETHYL METHACRYLATE COPOLYMER (SALUS AF); 2-(PERFLUOROHEXYL)ETHANOL; GLYCERIN; WATER; ALOE VERA LEAF

WhiskCare 373

Active Ingredient

Ethyl Alcohol 62% v/v

Purpose

Skin Sanitizer

Use

To help reduce the amount of bacteria on the skin

Warnings

Flammable. Keep away from fire or flame.

For external use only. If swallowed, seek medical attention.

When using this product do not use around or near the eyes. If contact occurs, flush eyes with water and contact a doctor immediately.

Stop use and consult a doctor when skin irritation appears and lasts.

KEEP OUT OF REACH OF CHILDREN.

Directions

- Pump a small amount of foam into palm of hand.
- Spread on hands and rub into skin until dry.
- Place a smaller amount into one hand and spread over both hands and wrists.
- Run into skin until dry.
- Children should be supervised while using this product.

Inactive Ingredients

Water, Acrylates/Perfluorohexylethyl Methacrylate Copolymer, Perfluorohexylethyl Alcohol, Glycerin, Aloe Barbadensis Leaf Juice